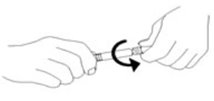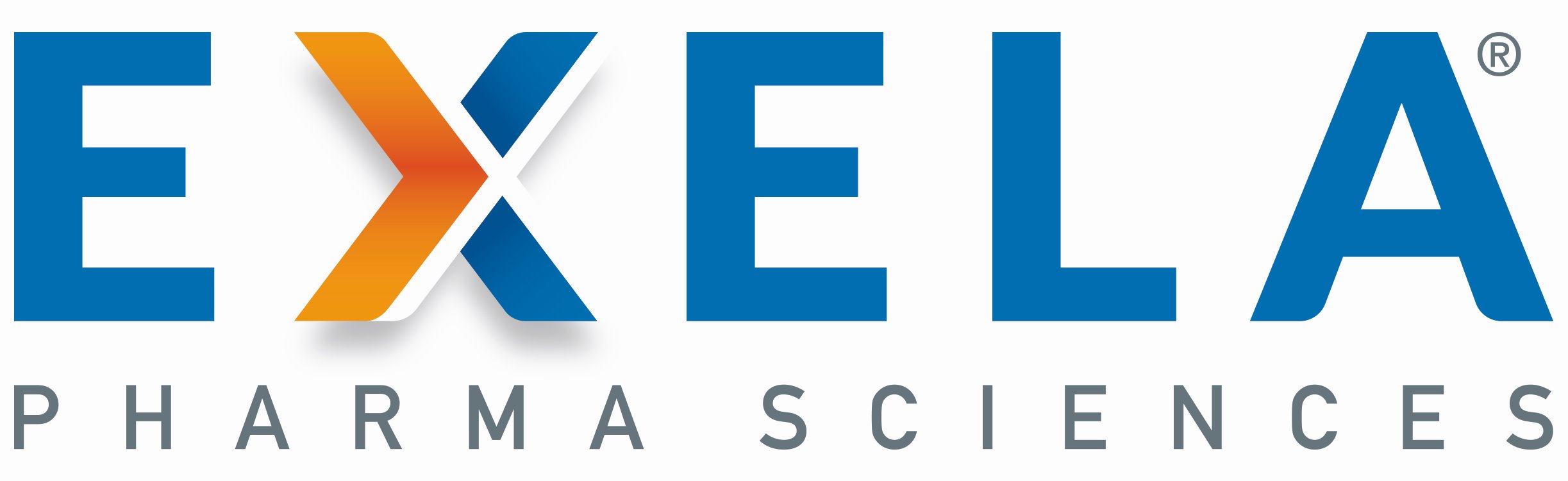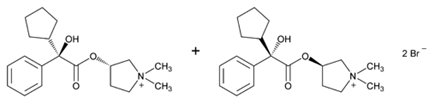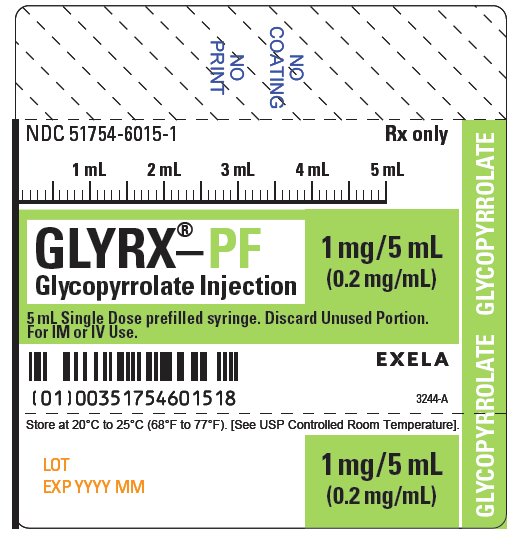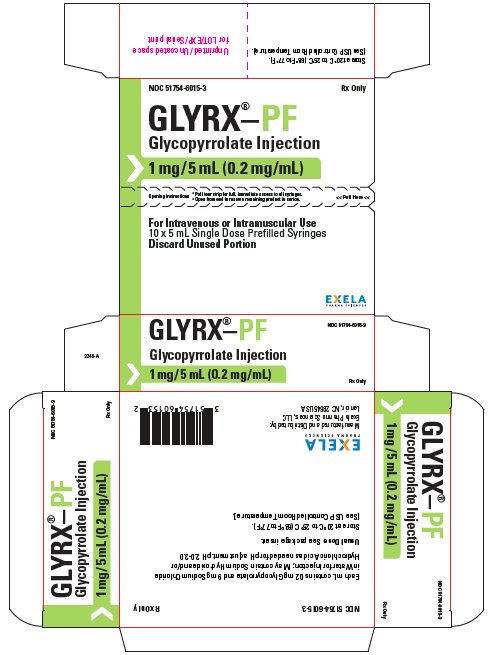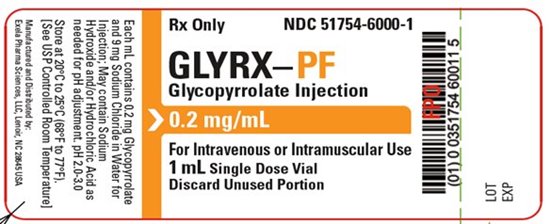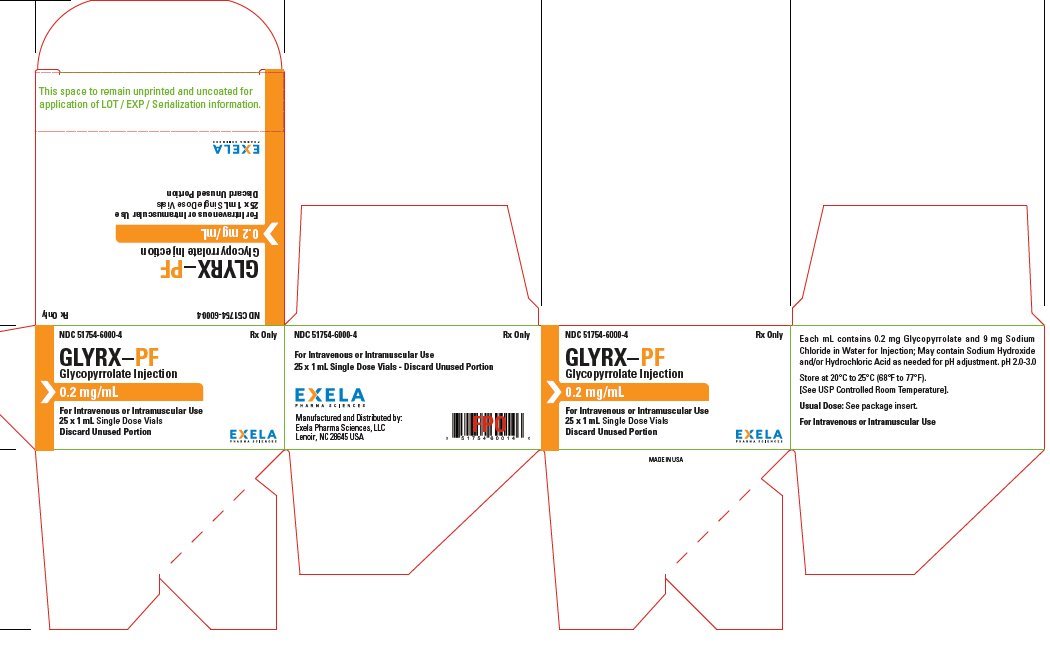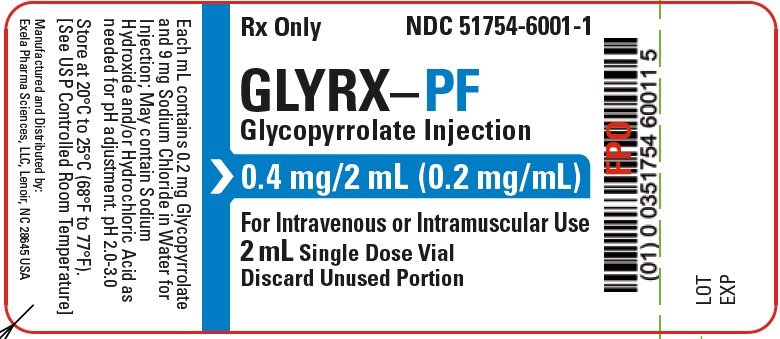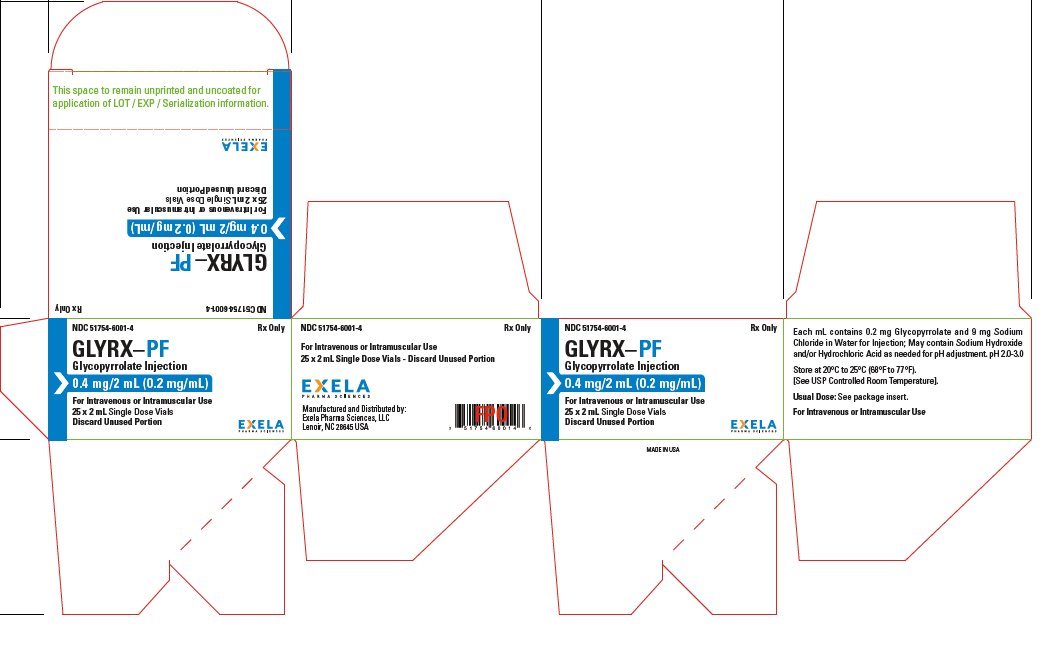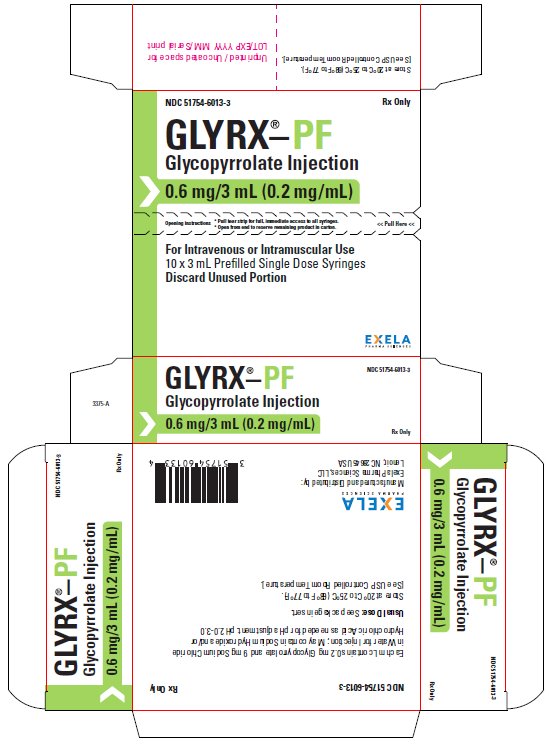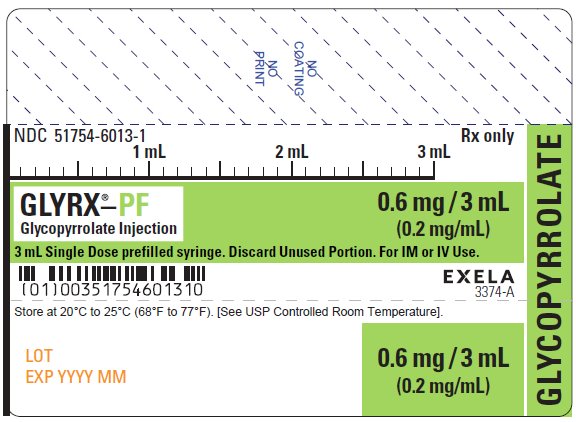 DRUG LABEL: GLYRX-PF
NDC: 51754-6015 | Form: INJECTION, SOLUTION
Manufacturer: Exela Pharma Sciences, LLC
Category: prescription | Type: HUMAN PRESCRIPTION DRUG LABEL
Date: 20250723

ACTIVE INGREDIENTS: GLYCOPYRROLATE 0.2 mg/1 mL
INACTIVE INGREDIENTS: WATER; SODIUM CHLORIDE

HIGHLIGHTS OF PRESCRIBING INFORMATION

These highlights do not include all the information needed to use GLYRX®-PF safely and effectively. See full prescribing information for GLYRX®-PF.
GLYRX®-PF (glycopyrrolate injection), for intravenous or intramuscular use
Initial U.S. Approval: 1975

RECENT MAJOR CHANGES

Indications and Usage (1)

1 INDICATIONS AND USAGE

GLYRX®-PF is an anticholinergic indicated:

in anesthesia (adult and pediatric patients)

- for reduction of airway or gastric secretions, and volume and acidity of gastric secretions, and blockade of cardiac inhibitory reflexes during induction of anesthesia and intubation,
- intraoperatively to counteract surgically or drug-induced or vagal reflex-associated arrhythmias, and
- for protection against peripheral muscarinic effects of cholinergic agents. (1)

in peptic ulcer (adults)

- To reduce symptoms of a peptic ulcer as an adjunct to treatment of peptic ulcer when rapid anticholinergic effect is desired or when oral medication is not tolerated.
- Limitations of Use
GLYRX-PF is not indicated as monotherapy for the treatment of peptic ulcer because effectiveness in peptic ulcer healing has not been established. (1)

2 DOSAGE AND ADMINISTRATION

GLYRX®-PF may be administered intramuscularly (IM), or intravenously (IV), with or without dilution, in the following indications. (2.1):

Adults (2.2)

Preanesthetic Medication: 0.004 mg/kg IM, given 30 to 60 minutes prior to the anticipated time of induction of anesthesia

Intraoperative Medication: single doses of 0.1 mg IV and repeated, as needed, at intervals of 2 to 3 minutes

Reversal of Neuromuscular Blockade: 0.2 mg for each 1 mg of neostigmine or 5 mg of pyridostigmine

Peptic Ulcer: 0.1 mg IV or IM at 4-hour intervals, 3 or 4 times daily

Pediatric patients (2.3)

Preanesthetic Medication: 0.004 mg/kg IM, given 30 to 60 minutes prior to the anticipated time of induction of anesthesia. Patients under 2 years of age may require up to 0.009 mg/kg

Intraoperative Medication: 0.004 mg/kg IV, not to exceed 0.1 mg in a single dose and repeated, as needed, at intervals of 2 to 3 minutes

Reversal of Neuromuscular Blockade: 0.2 mg for each 1 mg of neostigmine or 5 mg of pyridostigmine

Peptic Ulcer: GLYRX®-PF is not indicated for the treatment of peptic ulcer in pediatric patients

3 DOSAGE FORMS AND STRENGTHS

Injection: 0.2 mg/mL and 0.4 mg/2 mL (0.2 mg/mL) single-dose vial and 0.6 mg/3 mL and 1 mg/5 mL (0.2 mg/mL) single-dose prefilled syringe. (3)

4 CONTRAINDICATIONS

- Known hypersensitivity to glycopyrrolate or any of its inactive ingredients. (4)
- Peptic ulcer patients with glaucoma; obstructive uropathy; obstructive disease of the gastrointestinal tract; paralytic ileus, intestinal atony of the elderly, or debilitated patient; unstable cardiovascular status in acute hemorrhage; severe ulcerative colitis; toxic megacolon; complicating ulcerative colitis; myasthenia gravis. (4)

5 WARNINGS AND PRECAUTIONS

- Precipitation of Acute Glaucoma: Glycopyrrolate may cause mydriasis and increase intraocular pressure in patients with glaucoma. Advise patients with glaucoma to promptly seek medical care if they experience symptoms of acute angle closure glaucoma. (5.1)
- Drowsiness or Blurred Vision: May cause drowsiness or blurred vision. Advise patients not to drive or perform hazardous work until resolved. (5.2)
- Heat Prostration: Advise patients to avoid exertion and high environmental temperatures after receiving GLYRX®-PF. (5.3)
- Intestinal Obstruction: Diarrhea may be an early symptom of incomplete intestinal obstruction. Avoid use in patients with diarrhea and ileostomy or colostomy. (5.4)
- Tachycardia: Increase in heart rate may occur. Use with caution in patients with coronary artery disease, congestive heart failure, cardiac arrhythmias, hypertension, or hyperthyroidism. (5.5)

6 ADVERSE REACTIONS

Most common adverse reactions are related to anticholinergic pharmacology and may include xerostomia (dry mouth); urinary hesitancy and retention; blurred vision and photophobia due to mydriasis (dilation of the pupil); cycloplegia; increased ocular tension; tachycardia; bradycardia; palpitation; and decreased sweating. (6)

To report SUSPECTED ADVERSE REACTIONS, contact Exela Pharma Sciences, LLC at 1-888-451-4321 or FDA at 1-800-FDA-1088 or www.fda.gov/medwatch.

7 DRUG INTERACTIONS

Other anticholinergics or drugs with anticholinergic activity: May intensify the antimuscarinic effects and result in an increase in anticholinergic side effects. (7)

Potassium Chloride in a Wax Matrix: May increase severity of potassium chloride-induced gastrointestinal lesions. (7)

8 USE IN SPECIFIC POPULATIONS

Pediatric Use: Infants, patients with Down’s Syndrome, and pediatric patients with spastic paralysis or brain damage may experience an increased response to anticholinergics, thus increasing the potential for side effects. Large doses may cause hyperexcitability. (8.4).

FULL PRESCRIBING INFORMATION

1 INDICATIONS AND USAGE

GLYRX®-PF is indicated:

in anesthesia (all ages)

- for reduction of salivary, tracheobronchial, and pharyngeal secretions, reduction of volume and acidity of gastric secretions, and blockade of cardiac inhibitory reflexes during induction of anesthesia and intubation,
- intraoperatively to counteract surgically or drug-induced or vagal reflex-associated arrhythmias, and
- for protection against peripheral muscarinic effects of cholinergic agents such as neostigmine and pyridostigmine given to reverse the neuromuscular blockade due to non-depolarizing agents.

in peptic ulcer (adults)

- To reduce symptoms of a peptic ulcer as an adjunct to treatment of peptic ulcer when rapid anticholinergic effect is desired or when oral medication is not tolerated.
- Limitations of Use
  GLYRX-PF is not indicated as monotherapy for the treatment of peptic ulcer because effectiveness in peptic ulcer healing has not been established.

2 DOSAGE AND ADMINISTRATION

2.1 General Dosage and Administration Information

- Parenteral drug products should be inspected visually for particulate matter and discoloration prior to administration whenever solution and container permit.
- GLYRX®-PF may be administered intramuscularly or intravenously, with or without dilution.

2.2 Dosing in Adults

Preanesthetic Medication

The recommended dose of GLYRX®-PF is 0.004 mg/kg by intramuscular injection, given 30 to 60 minutes prior to the anticipated time of induction of anesthesia or at the time the preanesthetic narcotic and/or sedative are administered.

Intraoperative Medication

GLYRX®-PF may be used during surgery to counteract drug-induced or vagal reflexes and their associated arrhythmias (e.g., bradycardia). It should be administered intravenously as single doses of 0.1 mg and repeated, as needed, at intervals of 2 to 3 minutes. Attempt to determine the etiology of the arrhythmia, and perform the surgical or anesthetic manipulations necessary to correct parasympathetic imbalance.

Reversal of Neuromuscular Blockade

The recommended dose of GLYRX®-PF is 0.2 mg for each 1 mg of neostigmine or 5 mg of pyridostigmine. In order to minimize cardiac side effects, the drugs may be administered simultaneously by intravenous injection and may be mixed in the same syringe.

Peptic Ulcer

The usual recommended dose of GLYRX®-PF is 0.1 mg administered at 4-hour intervals, 3 or 4 times daily, intravenously or intramuscularly. Where more profound effect is required, 0.2 mg may be given. Some patients may need only a single dose. Frequency of administration should be dictated by patient response up to a maximum of four times daily.

2.3 Dosing in Pediatric Patients

Preanesthetic Medication

The recommended dose of GLYRX®-PF in pediatric patients is 0.004 mg/kg intramuscularly, given 30 to 60 minutes prior to the anticipated time of induction of anesthesia or at the time the preanesthetic narcotic and/or sedative are administered. Patients under 2 years of age, may require up to 0.009 mg/kg.

Intraoperative Medication

Because of the long duration of action of GLYRX®-PF if used as preanesthetic medication, additional GLYRX®-PF for anticholinergic effect intraoperatively is rarely needed; in the event it is required, the recommended pediatric dose is 0.004 mg/kg intravenously, not to exceed 0.1 mg in a single dose, which may be repeated, as needed, at intervals of 2 to 3 minutes. Attempt to determine the etiology of the arrhythmia, and perform the surgical or anesthetic manipulations necessary to correct parasympathetic imbalance.

Reversal of Neuromuscular Blockade

The recommended pediatric dose of GLYRX®-PF is 0.2 mg for each 1 mg of neostigmine or 5 mg of pyridostigmine. In order to minimize the appearance of cardiac side effects, the drugs may be administered simultaneously by intravenous injection and may be mixed in the same syringe.

Peptic Ulcer

GLYRX®-PF is not indicated for the treatment of peptic ulcer in pediatric patients.

2.4 Preparation and Handling

Diluent Compatibilities

Dextrose 5% and 10% in water, or saline, dextrose 5% in sodium chloride 0.45%, sodium chloride 0.9%, and Ringer’s Injection.

Diluent Incompatibilities

Lactated Ringer’s solution.

Admixture Compatibilities

Physical Compatibility

This list does not constitute an endorsement of the clinical utility or safety of co-administration of glycopyrrolate with these drugs. GLYRX®-PF is compatible for mixing and injection with the following injectable dosage forms: atropine sulfate, USP; physostigmine salicylate; diphenhydramine HCl; codeine phosphate, USP; benz-quinamide HCl; hydromorphone HCl, USP; droperidol; levorphanol tartrate; lidocaine, USP; meperidine HCl, USP; pyridostigmine bromide; morphine sulfate, USP; nalbuphine HCl; oxymorphone HCl; procaine HCl, USP; promethazine HCl, USP; neostigmine methylsulfate, USP; scopolamine HBr, USP; butorphanol tartrate; fentanyl citrate; trimethobenzamide HCl; and hydroxyzine HCl. GLYRX®-PF may be administered via the tubing of a running infusion of normal saline.

Admixture Incompatibilities

Physical Incompatibility

Because the stability of glycopyrrolate is questionable above a pH of 6.0 do not combine GLYRX®-PF in the same syringe with methohexital Na, chloramphenicol Na succinate, dimenhydrinate, pentobarbital Na, thiopental Na, secobarbital Na, sodium bicarbonate, diazepam, dexamethasone Na phosphate, or pentazocine lactate. These mixtures will result in a pH higher than 6.0 and may result in gas production or precipitation.

2.5 Instructions for Use of Prefilled Syringe

1. Perform visual inspection on the syringe by verifying:

- Absence of syringe damage
- Absence of external particles
- Absence of internal particles
- Proper drug color
- Drug name
- Drug strength
- Fill volume
- Route of administration
- Expiration date to be sure the drug has not expired

2. Do not remove the tamper evident seal. Push plunger rod slightly in to break the stopper lose while tip cap is still on

3. Remove tip cap and tamper evident seal by twisting off. (See Figure 1):

Figure 1.

4. Discard the tip cap.

5. Expel air bubble.

6. Adjust dose into sterile material (if applicable).

7. Connect the syringe to an appropriate intravenous connection.

- Before injection, ensure that the syringe is securely attached to the needle or needleless luer access device (NLAD).

8. Depress plunger rod to deliver medication. Ensure that pressure is maintained on the plunger rod during the entire administration.

9. Remove syringe from NLAD (if applicable) and discard into appropriate receptacle.

- To prevent needle stick injuries, do not recap needle when needle is connected to syringe.

NOTES:

All steps must be done sequentially

- Do not re-sterilize syringe
- Do not use this product on a sterile field
- Do not introduce any other fluid into the syringe at any time
- This product is for single dose only

3 DOSAGE FORMS AND STRENGTHS

GLYRX®-PF (glycopyrrolate injection) is a clear, colorless, solution for injection available as 0.2 mg/mL and 0.4 mg/2 mL (0.2 mg/mL) single-dose vials and as a 0.6 mg/3 mL and 1 mg/5 mL (0.2 mg/mL) single-dose prefilled syringe.

4 CONTRAINDICATIONS

GLYRX®-PF is contraindicated in:

- patients with known hypersensitivity to glycopyrrolate or any of its inactive ingredients.
- peptic ulcer patients with the following concurrent conditions: glaucoma; obstructive uropathy (for example, bladder neck obstruction due to prostatic hypertrophy); obstructive disease of the gastrointestinal tract (as in achalasia, pyloroduodenal stenosis, etc.); paralytic ileus, intestinal atony of the elderly or debilitated patient; unstable cardiovascular status in acute hemorrhage; severe ulcerative colitis; toxic megacolon complicating ulcerative colitis; myasthenia gravis.

5 WARNINGS AND PRECAUTIONS

5.1 Precipitation of Acute Glaucoma

Glycopyrrolate may cause mydriasis and increase intraocular pressure in patients with glaucoma. Advise patients with glaucoma to promptly seek medical care in the event that they experience symptoms of acute angle closure glaucoma (pain and reddening of the eyes, accompanied by dilated pupils).

5.2 Drowsiness or Blurred Vision

GLYRX®-PF may cause drowsiness or blurred vision. Warn patients not to participate in activities requiring mental alertness, such as operating a motor vehicle or other machinery, or performing hazardous work, until these issues resolve.

5.3 Heat Prostration

In the presence of fever, high environmental temperature, and/or during physical exercise, heat prostration can occur with use of anticholinergic agents including GLYRX®-PF (due to decreased sweating), particularly in children and the elderly. Advise patients to avoid exertion and high environmental temperature after receiving GLYRX®-PF.

5.4 Intestinal Obstruction

Diarrhea may be an early symptom of incomplete intestinal obstruction, especially in patients with ileostomy or colostomy. In this instance treatment with GLYRX®-PF is inappropriate and possibly harmful. Avoid use in patients with these conditions.

5.5 Tachycardia

Investigate any tachycardia before giving GLYRX®-PF because an increase in the heart rate may occur. Use with caution in patients with coronary artery disease, congestive heart failure, cardiac arrhythmias, hypertension, or hyperthyroidism.

5.6 Risk of Use in Patients with Renal Impairment

Renal elimination of glycopyrrolate may be severely impaired in patients with renal failure. Dosage adjustments may be necessary in this population [see Clinical Pharmacology (12.3)].

5.7 Autonomic Neuropathy, Hepatic Disease, Ulcerative Colitis, Prostatic Hypertrophy, or Hiatal Hernia

Use GLYRX®-PF with caution in the elderly and in all patients with autonomic neuropathy, hepatic disease, ulcerative colitis, prostatic hypertrophy, or hiatal hernia, because anticholinergic drugs may aggravate these conditions. Consider dose reduction and closely monitor the elderly and patients with autonomic neuropathy, hepatic disease, ulcerative colitis, prostatic hypertrophy, or hiatal hernia.

5.8 Delayed Gastric Emptying/Gastric Stasis

The use of anticholinergic drugs, including GLYRX®-PF, in the treatment of peptic ulcer may produce a delay in gastric emptying/gastric stasis. Monitor patients for symptoms such as vomiting, dyspepsia, early satiety, abdominal distention, and increased abdominal pain. Discontinue GLYRX®-PF treatment if these symptoms develop or worsen on treatment.

5.9 Light Sensitivity

Patients may experience sensitivity of the eyes to light. Advise patients to protect their eyes from light after receiving GLYRX®-PF.

6 ADVERSE REACTIONS

The following adverse reactions were identified in clinical studies or postmarketing reports. Because some of these reactions were reported voluntarily from a population of uncertain size, it is not always possible to reliably estimate their frequency or establish a causal relationship to drug exposure.

Adverse reactions to anticholinergics include xerostomia (dry mouth); urinary hesitancy and retention; blurred vision and photophobia due to mydriasis (dilation of the pupil); cycloplegia; increased ocular tension; tachycardia; palpitation; decreased sweating; loss of taste; headache; nervousness; drowsiness; weakness; dizziness; insomnia; nausea; vomiting; impotence; suppression of lactation; constipation; bloated feeling; severe allergic reactions including anaphylactic/anaphylactoid reactions; hypersensitivity; urticaria, pruritus, dry skin, and other dermal manifestations; some degree of mental confusion and/or excitement, especially in elderly persons.

The following adverse reactions have been reported from post-marketing experience with glycopyrrolate: malignant hyperthermia; cardiac arrhythmias (including bradycardia, ventricular tachycardia, ventricular fibrillation); cardiac arrest; hypertension; hypotension; seizures; and respiratory arrest. Post-marketing reports have included cases of heart block and QTc interval prolongation associated with the combined use of glycopyrrolate and an anticholinesterase. Injection site reactions including pruritus, edema, erythema, and pain have also been reported.

7 DRUG INTERACTIONS

The concurrent use of GLYRX®-PF with other anticholinergics or medications with anticholinergic activity, such as phenothiazines, antiparkinson drugs, or tricyclic antidepressants, may intensify the antimuscarinic effects and result in an increase in anticholinergic side effects.

Concomitant administration of GLYRX®-PF and potassium chloride in a wax matrix may increase the severity of potassium chloride-induced gastrointestinal lesions as a result of a slower gastrointestinal transit time.

8 USE IN SPECIFIC POPULATIONS

8.1 Pregnancy

Risk Summary

Limited data available with glycopyrrolate use during pregnancy have not identified a drug-associated risk of birth defects and miscarriage, however, most of the reported exposures occurred after the first trimester. Most of the available data are based on studies with exposures that occurred at the time of Cesarean-section delivery, and these studies have not identified an adverse effect on maternal outcomes or infant Apgar scores (see Data).

In animal reproduction studies in pregnant rats and rabbits administered glycopyrrolate orally (rats) and intramuscularly (rabbits) during the period of organogenesis, no teratogenic effects were seen at 640-times and 10-times the maximum recommended human dose (MRHD) of 1 mg (on a mg/m^2 basis), respectively (see Data).

The estimated background risk for major birth defects and miscarriage for the indicated population is unknown. All pregnancies have a background risk of birth defect, loss, or other adverse outcomes. In the U.S. general population, the estimated background risk of major birth defects and miscarriage in the clinically recognized pregnancies is 2-4% and 15−20%, respectively.

Data

Human Data

Published, randomized, controlled trials over several decades, which compared the use of glycopyrrolate to another antimuscarinic agent in pregnant women during Cesarean section, have not identified adverse maternal or infant outcomes. In normal doses (0.004 mg/kg), glycopyrrolate does not appear to affect fetal heart rate or fetal heart rate variability to a significant degree. Concentrations of glycopyrrolate in umbilical venous and arterial blood and in the amniotic fluid are low after intramuscular administration to parturients. Therefore, glycopyrrolate does not appear to penetrate through the placental barrier in significant amounts.

There are no studies on the safety of glycopyrrolate exposure during the period of organogenesis, and therefore, it is not possible to draw any conclusions on the risk of birth defects following exposure to glycopyrrolate during pregnancy. In addition, there are no data on the risk of miscarriage following fetal exposure to glycopyrrolate.

Animal Data

Reproduction studies with glycopyrrolate were performed in rats at a dietary dose of approximately 65 mg/kg/day (exposure was approximately 640 times the maximum recommended daily human dose of 1 mg on a mg/m^2 basis) and rabbits at intramuscular doses of up to 0.5 mg/kg/day (exposure was approximately 10 times the maximum recommended daily human dose on a mg/m^2 basis). These studies produced no teratogenic effects to the fetus.

A preclinical study on reproductive performance of rats given glycopyrrolate resulted in a decreased rate of conception and survival at weaning.

8.2 Lactation

Risk Summary

There are no data on the presence of glycopyrrolate in either human milk or animal milk, the effects on the breastfed infant, or the effects on milk production. As with other anticholinergics, glycopyrrolate may cause suppression of lactation [see Adverse Reactions (6)]. The developmental and health benefits of breast feeding should be considered along with the mother’s clinical need for Glycopyrrolate Injection and any potential adverse effects on the breastfed child from Glycopyrrolate Injection or from the underlying maternal condition.

8.4 Pediatric Use

Safety and effectiveness in pediatric patients have not been established for the management of peptic ulcer.

Dysrhythmias associated with the use of glycopyrrolate intravenously as a premedicant or during anesthesia have been observed in pediatric patients.

Infants, patients with Down’s syndrome, and pediatric patients with spastic paralysis or brain damage may experience an increased response to anticholinergics, thus increasing the potential for side effects.

A paradoxical reaction characterized by hyperexcitability may occur in pediatric patients receiving large doses of anticholinergics including GLYRX®-PF. Infants and young children are especially susceptible to the toxic effects of anticholinergics.

8.5 Geriatric Use

Clinical Studies of GLYRX®-PF did not include sufficient numbers of subjects aged 65 and over to determine whether they respond differently from younger subjects. Other reported clinical experience has not identified differences in responses between the elderly and younger patients. In general, dose selection for an elderly patient should be cautious, usually starting at the low end of the dosing range, reflecting the greater frequency of decreased hepatic, renal, or cardiac function, and of concomitant disease or other therapy.

8.6 Renal Impairment

Renal elimination of glycopyrrolate may be severely impaired in patients with renal failure. Dosage adjustments may be necessary [see Clinical Pharmacology (12.3)].

10 OVERDOSAGE

To combat peripheral anticholinergic effects, a quaternary ammonium anticholinesterase such as neostigmine methylsulfate (which does not cross the blood-brain barrier) may be given intravenously in increments of 0.25 mg in adults. This dosage may be repeated every five to ten minutes until anticholinergic overactivity is reversed or up to a maximum of 2.5 mg. Proportionately smaller doses should be used in pediatric patients. Indication for repetitive doses of neostigmine should be based on close monitoring of the decrease in heart rate and the return of bowel sounds.

If CNS symptoms (e.g., excitement, restlessness, convulsions, psychotic behavior) occur, physostigmine (which does cross the blood–brain barrier) may be used. Physostigmine 0.5 to 2 mg should be slowly administered intravenously and repeated as necessary up to a total of 5 mg in adults. Proportionately smaller doses should be used in pediatric patients.

To combat hypotension, administer IV fluids and/or pressor agents along with supportive care. Fever should be treated symptomatically.

Following overdosage, a curare-like action may occur, i.e., neuromuscular blockade leading to muscular weakness and possible paralysis. In the event of a curare-like effect on respiratory muscles, artificial respiration should be instituted and maintained until effective respiratory action returns.

11 DESCRIPTION

GLYRX®-PF is a synthetic anticholinergic agent. It is intended for intramuscular or intravenous administration. Each 1 mL of GLYRX®-PF contains 0.2 mg of glycopyrrolate, water for injection, sodium chloride as a tonicity agent, and hydrochloric acid or sodium hydroxide as pH adjusters. GLYRX®-PF is preservative free.

Glycopyrrolate is a quaternary ammonium salt with the following chemical name: (RS)-[3-(SR)-Hydroxy-1,1-dimethylpyrrolidinium bromide] α-cyclopentylmandelate. The molecular formula is C19H28BrNO3 and the molecular weight is 398.34. Glycopyrrolate structural formula is as follows:

Glycopyrrolate occurs as a white, odorless, crystalline powder. It is soluble in water and alcohol, and practically insoluble in chloroform and ether. It is completely ionized at physiological pH values. GLYRX®-PF is a clear, colorless, sterile liquid with a pH of 2.0 – 3.0. The partition coefficient of Glycopyrrolate in n-octanol/water system is 0.304 (log10 P = -1.52) at ambient room temperature (24°C).

12 CLINICAL PHARMACOLOGY

12.1 Mechanism of Action

Glycopyrrolate, like other anticholinergic (antimuscarinic) agents, inhibits the action of acetylcholine on structures innervated by postganglionic cholinergic nerves and on smooth muscles that respond to acetylcholine but lack cholinergic innervation. These peripheral cholinergic receptors are present in the autonomic effector cells of smooth muscle, cardiac muscle, the sinoatrial node, the atrioventricular node, exocrine glands and, to a limited degree, in the autonomic ganglia. Thus, it diminishes the volume and free acidity of gastric secretions and controls excessive pharyngeal, tracheal, and bronchial secretions.

12.2 Pharmacodynamics

Glycopyrrolate antagonizes muscarinic symptoms (e.g., bronchorrhea, bronchospasm, bradycardia, and intestinal hypermotility) induced by cholinergic drugs such as the anticholinesterases. The highly polar quaternary ammonium group of glycopyrrolate limits its passage across lipid membranes, such as the blood-brain barrier, in contrast to atropine sulfate and scopolamine hydrobromide, which are highly non-polar tertiary amines which penetrate lipid barriers easily. For this reason, the occurrence of CNS-related side effects is lower, in comparison to their incidence following administration of anticholinergics which are chemically tertiary amines that can cross this barrier readily. With intravenous injection, the onset of action is generally evident within one minute. Following intramuscular administration, the onset of action is noted in 15 to 30 minutes, with peak effects occurring within approximately 30 to 45 minutes. The vagal blocking effects persist for 2 to 3 hours and the antisialagogue effects persist up to 7 hours, periods longer than for atropine.

12.3 Pharmacokinetics

The following pharmacokinetic information and conclusions were obtained from published studies that used nonspecific assay methods.

Distribution

The mean volume of distribution of glycopyrrolate was estimated to be 0.42 ± 0.22 L/kg.

Elimination

Metabolism

The in vivo metabolism of glycopyrrolate in humans has not been studied.

Excretion

The mean clearance and mean t1/2 values were reported to be 0.54 ± 0.14 L/kg/hr and 0.83 ± 0.27 hr, respectively post IV administration. After IV administration of a 0.2 mg radiolabeled glycopyrrolate, 85% of dose recovered was recovered in urine 48 hours post dose and some of the radioactivity was also recovered in bile. After IM administration of glycopyrrolate to adults, the mean t1/2 value is reported to be between 0.55 to 1.25 hrs. Over 80% of IM dose administered was recovered in urine and the bile as unchanged drug and half the IM dose is excreted within 3 hrs. The following table summarizes the mean and standard deviation of pharmacokinetic parameters from a study.

Group | t1/2 | Vss | CL | Tmax | Cmax | AUC
Group | (hr) | (L/kg) | (L/kg/hr) | (min) | (µg/L) | (µg/L•hr)
(6 µg/kg IV) | 0.83 ± 0.27 | 0.42 ± 0.22 | 0.54 ± 0.14 | – | – | 8.64 ± 1.49 [0-8 hr]
(8 µg/kg IM) | – | – | – | 27.48 ± 6.12 | 3.47 ± 1.48 | 6.64 ± 2.33

Specific Populations

Pediatric Patients:

Following IV administration (5 μg/kg glycopyrrolate) to infants and children, the mean t1/2 values were reported to be between 21.6 and 130.0 minutes and between 19.2 and 99.2 minutes, respectively.

Patients with Renal Impairment:

In one study Glycopyrrolate was administered IV in uremic patients undergoing renal transplantation. The mean elimination half-life was significantly longer (46.8 minutes) than in healthy patients (18.6 minutes). The mean area-under-the-concentration-time curve (10.6 hr-μg/L), mean plasma clearance (0.43 L/hr/kg), and mean 3-hour urine excretion (0.7%) for Glycopyrrolate were also significantly different than those of controls (3.73 hr-μg/L, 1.14 L/hr/kg, and 50%, respectively). These results suggest that the elimination of glycopyrrolate is severely impaired in patients with renal failure.

13 NONCLINICAL TOXICOLOGY

13.1 Carcinogenesis, Mutagenesis and Impairment of Fertility

Carcinogenesis

Long-term studies in animals have not been performed to evaluate carcinogenic potential.

Mutagenesis

Studies to evaluate the mutagenic potential of glycopyrrolate have not been conducted.

Impairment of Fertility

In reproduction studies in rats, dietary administration of glycopyrrolate resulted in diminished rates of conception in a dose-related manner. Other studies in dogs suggest that this may be due to diminished seminal secretion which is evident at high doses of glycopyrrolate.

16 HOW SUPPLIED, STORAGE AND HANDLING

GLYRX®-PF (glycopyrrolate injection) is available in:

0.2 mg/mL single-dose vials packaged in 25s (NDC 51754-6000-4)

0.4 mg/2 mL (0.2 mg/mL) single-dose vials packaged in 25s (NDC 51754-6001-4)

0.6 mg/3 mL (0.2 mg/mL) single-dose prefilled disposable syringes packaged in 10s (NDC 51754-6013-3)

1 mg/5 mL (0.2 mg/mL) single-dose prefilled disposable syringes packaged in 10s (NDC 51754-6015-3)

Store at 20°C to 25°C (68°F to 77°F); excursions permitted to 15°C to 30°C (59°F to 86°F). [See USP Controlled Room Temperature].

17 PATIENT COUNSELING INFORMATION

Drowsiness or Blurred Vision: Inform patients that GLYRX®-PF may cause drowsiness or blurred vision. Warn patients not to operate a motor vehicle or other machinery or perform hazardous work until these issues resolve [see Warnings and Precautions (5.2)].

Heat Prostration: Inform patients that in the presence of fever, high environmental temperature and/or during physical exercise, heat prostration can occur with use of anticholinergic agents, including GLYRX®-PF (due to decreased sweating), particularly in children and the elderly. Advise patients to avoid exertion and high environmental temperature after receiving GLYRX®-PF [see Warnings and Precautions (5.3)].

Light Sensitivity: Advise patients that glycopyrrolate injection may cause sensitivity of the eyes to light and to protect their eyes from light after receiving GLYRX®-PF [see Warnings and Precautions (5.9)].

Drug Interactions: Inform patients that GLYRX®-PF may interact with other drugs. Advise patients to report to their healthcare provider the use of any other medication [see Drug Interactions (7)].

Manufactured and Distributed by:

Exela Pharma Sciences, LLC

Lenoir, NC 28645

PACKAGE/LABEL PRINCIPAL DISPLAY PANEL- 3 mL Syringe Label

NDC 51754-6013-1 Rx only

GLYRX®-PF

Glycopyrrolate Injection 0.6 mg/3 mL

(0.2 mg/mL)

3 mL Single Dose prefilled syringe. Discard Unused Portion. For IM or IV Use.

Store at 20°C to 25°C (68°F to 77°F). [See USP Controlled Room Temperature

PACKAGE/LABEL PRINCIPAL DISPLAY PANEL- 3 mL Syringe Carton

NDC 51754-6013-3 Rx only

GLYRX®-PF

Glycopyrrolate Injection

0.6 mg/3 mL (0.2 mg/mL)

For Intravenous or Intramuscular Use

10 x 3 mL Single Dose Prefilled Syringes

Discard Unused Portion

PACKAGE/LABEL PRINCIPAL DISPLAY PANEL-5 mL Syringe Label

NDC 51754-6015-1 Rx Only

GLYRX®-PF

Glycopyrrolate Injection 1 mg/5 mL

(0.2 mg/mL)

5 mL Single Dose prefilled syringe. Discard Unused Portion.

For IM or IV Use.

Store at 20°C to 25°C (68°F to 77°F). [See USP Controlled Room Temperature]

PACKAGE/LABEL PRINCIPAL DISPLAY PANEL- 5 mL Syringe Carton

NDC 51754-6015-3 Rx Only

GLYRX®-PF

Glycopyrrolate Injection

1 mg/5 mL (0.2 mg/mL)

For Intravenous or Intramuscular Use

10 x 5 mL Single Dose Prefilled Syringes

Discard Unused Portion

PACKAGE/LABEL PRINCIPAL DISPLAY PANEL- 1 mL Vial Label

Rx Only NDC 51754-6000-1

GLYRX-PF

Glycopyrrolate Injection

0.2 mg/mL

For Intravenous or Intramuscular Use

1 mL Single Dose Vial

Discard Unused Portion

PACKAGE/LABEL PRINCIPAL DISPLAY PANEL- 1 mL Carton

Rx Only NDC 51754-6000-4

GLYRX-PF

Glycopyrrolate Injection

0.2 mg/mL

For Intravenous or Intramuscular Use

25 x 1 mL Single Dose Vials

Discard Unused Portion

Exela Pharma Sciences, LLC

PACKAGE/LABEL PRINCIPAL DISPLAY PANEL-2 mL Vial Label

Rx Only NDC 51754-6001-1

GLYRX-PF

Glycopyrrolate Injection

0.4 mg/2 mL (0.2 mg/mL)

For Intravenous or Intramuscular Use

2 mL Single Dose Vial

Discard Unused Portion

PACKAGE/LABEL PRINCIPAL DISPLAY PANEL- 2 mL Vial Carton

Rx Only NDC 51754-6001-4

GLYRX-PF

Glycopyrrolate Injection

0.4 mg/2 mL

For Intravenous or Intramuscular Use

25 x 2 mL Single Dose Vials

Discard Unused Portion

Exela Pharma Sciences, LLC